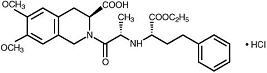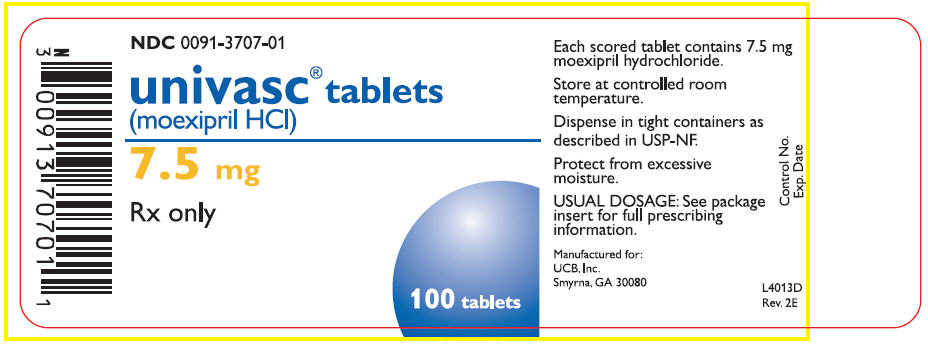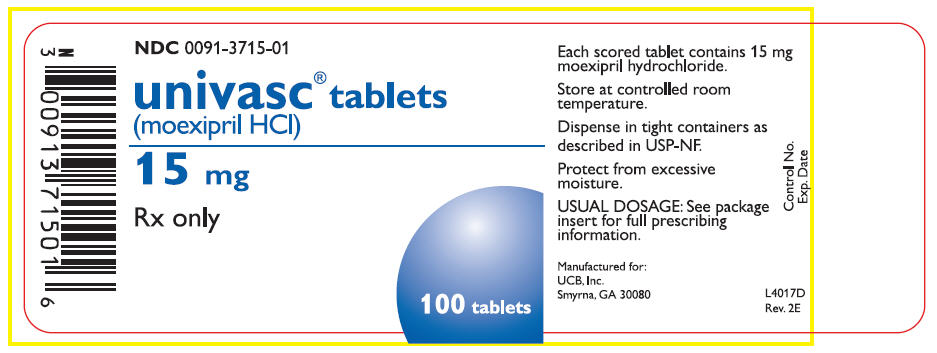 DRUG LABEL: Univasc
NDC: 0091-3707 | Form: TABLET, FILM COATED
Manufacturer: UCB, Inc.
Category: prescription | Type: HUMAN PRESCRIPTION DRUG LABEL
Date: 20160223

ACTIVE INGREDIENTS: MOEXIPRIL HYDROCHLORIDE 7.5 mg/1 1
INACTIVE INGREDIENTS: LACTOSE; MAGNESIUM OXIDE; CROSPOVIDONE; MAGNESIUM STEARATE; GELATIN; HYDROXYPROPYL CELLULOSE (TYPE H); HYPROMELLOSES; POLYETHYLENE GLYCOL 6000; TITANIUM DIOXIDE; FERRIC OXIDE RED

univasc® tablets
(moexipril hydrochloride)

Rx only

WARNING

FETAL TOXICITY

See full prescribing information for complete boxed warning.

- When pregnancy is detected, discontinue univasc® as soon as possible.
- Drugs that act directly on the renin-angiotensin system can cause injury and death to the developing fetus. See WARNINGS: Fetal Toxicity

DESCRIPTION

univasc® (moexipril hydrochloride), the hydrochloride salt of moexipril, has the empirical formula C27H34N2O7•HCl and a molecular weight of 535.04. It is chemically described as [3S-[2[R*(R*)],3R*]]-2-[2-[[1-(ethoxycarbonyl)-3-phenylpropyl]amino]-1-oxopropyl]-1,2,3,4-tetrahydro-6,7-dimethoxy-3-isoquinolinecarboxylic acid, monohydrochloride. It is a non-sulfhydryl containing precursor of the active angiotensin-converting enzyme (ACE) inhibitor moexiprilat and its structural formula is:

Moexipril hydrochloride is a fine white to off-white powder. It is soluble (about 10% weight-to-volume) in distilled water at room temperature.

univasc® is supplied as scored, coated tablets containing 7.5 mg and 15 mg of moexipril hydrochloride for oral administration. In addition to the active ingredient, moexipril hydrochloride, the tablet core contains the following inactive ingredients: lactose, magnesium oxide, crospovidone, magnesium stearate and gelatin. The film coating contains hydroxypropyl cellulose, hypromellose, polyethylene glycol 6000, magnesium stearate, titanium dioxide, and ferric oxide.

CLINICAL PHARMACOLOGY

Mechanism of Action

Moexipril hydrochloride is a prodrug for moexiprilat, which inhibits ACE in humans and animals. The mechanism through which moexiprilat lowers blood pressure is believed to be primarily inhibition of ACE activity. ACE is a peptidyl dipeptidase that catalyzes the conversion of the inactive decapeptide angiotensin I to the vasoconstrictor substance angiotensin II. Angiotensin II is a potent peripheral vasoconstrictor that also stimulates aldosterone secretion by the adrenal cortex and provides negative feedback on renin secretion. ACE is identical to kininase II, an enzyme that degrades bradykinin, an endothelium-dependent vasodilator. Moexiprilat is about 1000 times as potent as moexipril in inhibiting ACE and kininase II. Inhibition of ACE results in decreased angiotensin II formation, leading to decreased vasoconstriction, increased plasma renin activity, and decreased aldosterone secretion. The latter results in diuresis and natriuresis and a small increase in serum potassium concentration (mean increases of about 0.25 mEq/L were seen when moexipril was used alone, see PRECAUTIONS).

Whether increased levels of bradykinin, a potent vasodepressor peptide, play a role in the therapeutic effects of moexipril remains to be elucidated. Although the principal mechanism of moexipril in blood pressure reduction is believed to be through the renin-angiotensin-aldosterone system, ACE inhibitors have some effect on blood pressure even in apparent low-renin hypertension. As is the case with other ACE inhibitors, however, the antihypertensive effect of moexipril is considerably smaller in black patients, a predominantly low-renin population, than in non-black hypertensive patients.

Pharmacokinetics and Metabolism

Pharmacokinetics

Moexipril's antihypertensive activity is almost entirely due to its deesterified metabolite, moexiprilat. Bioavailability of oral moexipril is about 13% compared to intravenous (I.V.) moexipril (both measuring the metabolite moexiprilat), and is markedly affected by food, which reduces the peak plasma level (Cmax) and AUC (see Absorption). Moexipril should therefore be taken in a fasting state. The time of peak plasma concentration (Tmax) of moexiprilat is about 1½ hours and elimination half-life (t½) is estimated at 2 to 9 hours in various studies, the variability reflecting a complex elimination pattern that is not simply exponential. Like all ACE inhibitors, moexiprilat has a prolonged terminal elimination phase, presumably reflecting slow release of drug bound to the ACE. Accumulation of moexiprilat with repeated dosing is minimal, about 30%, compatible with a functional elimination t½ of about 12 hours. Over the dose range of 7.5 to 30 mg, pharmacokinetics are approximately dose proportional.

Absorption

Moexipril is incompletely absorbed, with bioavailability as moexiprilat of about 13%. Bioavailability varies with formulation and food intake which reduces Cmax and AUC by about 70% and 40% respectively after the ingestion of a low-fat breakfast or by 80% and 50% respectively after the ingestion of a high-fat breakfast.

Distribution

The clearance (CL) for moexipril is 441 mL/min and for moexiprilat 232 mL/min with a t½ of 1.3 and 9.8 hours, respectively. Moexiprilat is about 50% protein bound. The volume of distribution of moexiprilat is about 183 liters.

Metabolism and Excretion

Moexipril is relatively rapidly converted to its active metabolite moexiprilat, but persists longer than some other ACE inhibitor prodrugs, such that its t½ is over one hour and it has a significant AUC. Both moexipril and moexiprilat are converted to diketopiperazine derivatives and unidentified metabolites. After I.V. administration of moexipril, about 40% of the dose appears in urine as moexiprilat, about 26% as moexipril, with small amounts of the metabolites; about 20% of the I.V. dose appears in feces, principally as moexiprilat. After oral administration, only about 7% of the dose appears in urine as moexiprilat, about 1% as moexipril, with about 5% as other metabolites. Fifty-two percent of the dose is recovered in feces as moexiprilat and 1% as moexipril.

Special Populations

Decreased Renal Function

The effective elimination t½ and AUC of both moexipril and moexiprilat are increased with decreasing renal function. There is insufficient information available to characterize this relationship fully, but at creatinine clearances in the range of 10 to 40 mL/min, the t½ of moexiprilat is increased by a factor of 3 to 4.

Decreased Hepatic Function

In patients with mild to moderate cirrhosis given single 15 mg doses of moexipril, the Cmax of moexipril was increased by about 50% and the AUC increased by about 120%, while the Cmax for moexiprilat was decreased by about 50% and the AUC increased by almost 300%.

Elderly Patients

In elderly male subjects (65-80 years old) with clinically normal renal and hepatic function, the AUC and Cmax of moexiprilat is about 30% greater than those of younger subjects (19-42 years old).

Pharmacokinetic Interactions With Other Drugs

No clinically important pharmacokinetic interactions occurred when univasc® was administered concomitantly with hydrochlorothiazide, digoxin, or cimetidine.

Pharmacodynamics and Clinical Effect

Single and multiple doses of 15 mg or more of univasc® gives sustained inhibition of plasma ACE activity of 80-90%, beginning within 2 hours and lasting 24 hours (80%).

In controlled trials, the peak effects of orally administered moexipril increased with the dose administered over a dose range of 7.5 to 60 mg, given once a day. Antihypertensive effects were first detectable about 1 hour after dosing, with a peak effect between 3 and 6 hours after dosing. Just before dosing (i.e., at trough), the antihypertensive effects were less prominently related to dose and the antihypertensive effect tended to diminish during the 24-hour dosing interval when the drug was administered once a day.

In multiple dose studies in the dose range of 7.5 to 30 mg once daily, univasc® lowered sitting diastolic and systolic blood pressure effects at trough by 3 to 6 mmHg and 4 to 11 mmHg more than placebo, respectively. There was a tendency toward increased response with higher doses over this range. These effects are typical of ACE inhibitors but, to date, there are no trials of adequate size comparing moexipril with other antihypertensive agents.

The trough diastolic blood pressure effects of moexipril were approximately 3 to 6 mmHg in various studies. Generally, higher doses of moexipril leave a greater fraction of the peak blood pressure effect still present at trough. During dose titration, any decision as to the adequacy of a dosing regimen should be based on trough blood pressure measurements. If diastolic blood pressure control is not adequate at the end of the dosing interval, the dose can be increased or given as a divided (BID) regimen.

During chronic therapy, the antihypertensive effect of any dose of univasc® is generally evident within 2 weeks of treatment, with maximal reduction after 4 weeks. The antihypertensive effects of univasc® have been proven to continue during therapy for up to 24 months.

univasc®, like other ACE inhibitors, is less effective in decreasing trough blood pressures in blacks than in non-blacks. Placebo-corrected trough group mean diastolic blood pressure effects in blacks in the proposed dose range varied between +1 to -3 mmHg compared with responses in non-blacks of -4 to -6 mmHg.

The effectiveness of univasc® was not significantly influenced by patient age, gender, or weight. univasc® has been shown to have antihypertensive activity in both pre- and postmenopausal women who have participated in placebo-controlled clinical trials.

Formal interaction studies with moexipril have not been carried out with antihypertensive agents other than thiazide diuretics. In these studies, the added effect of moexipril was similar to its effect as monotherapy. In general, ACE inhibitors have less than additive effects with beta-adrenergic blockers, presumably because both work by inhibiting the renin-angiotensin system.

INDICATIONS AND USAGE

univasc® is indicated for treatment of patients with hypertension. It may be used alone or in combination with thiazide diuretics.

In using univasc®, consideration should be given to the fact that another ACE inhibitor, captopril, has caused agranulocytosis, particularly in patients with renal impairment or collagen-vascular disease. Available data are insufficient to show that univasc® does not have a similar risk (see WARNINGS).

In considering use of univasc®, it should be noted that in controlled trials ACE inhibitors have an effect on blood pressure that is less in black patients than in non-blacks. In addition, ACE inhibitors (for which adequate data are available) cause a higher rate of angioedema in black than in non-black patients (see WARNINGS, Angioedema).

CONTRAINDICATIONS

univasc® is contraindicated in patients who are hypersensitive to this product and in patients with a history of angioedema related to previous treatment with an ACE inhibitor.

Do not co-administer aliskiren with univasc® in patients with diabetes (see PRECATIONS, Drug Interactions).

WARNINGS

Anaphylactoid and Possibly Related Reactions

Presumably because angiotensin-converting enzyme inhibitors affect the metabolism of eicosanoids and polypeptides, including endogenous bradykinin, patients receiving ACE inhibitors, including univasc®, may be subject to a variety of adverse reactions, some of them serious.

Head and Neck Angioedema

Angioedema involving the face, extremities, lips, tongue, glottis, and/or larynx has been reported in patients treated with ACE inhibitors, including univasc®. Symptoms suggestive of angioedema or facial edema occurred in <0.5% of moexipril-treated patients in placebo-controlled trials. None of the cases were considered life-threatening and all resolved either without treatment or with medication (antihistamines or glucocorticoids). One patient treated with hydrochlorothiazide alone experienced laryngeal edema. No instances of angioedema were reported in placebo-treated patients.

In cases of angioedema, treatment should be promptly discontinued and the patient carefully observed until the swelling disappears. In instances where swelling has been confined to the face and lips, the condition has generally resolved without treatment, although antihistamines have been useful in relieving symptoms.

Angioedema associated with involvement of the tongue, glottis, or larynx, may be fatal due to airway obstruction. Appropriate therapy, e.g., subcutaneous epinephrine solution 1:1000 (0.3 to 0.5 mL) and/or measures to ensure a patent airway, should be promptly provided (see ADVERSE REACTIONS).

Intestinal Angioedema

Intestinal angioedema has been reported in patients treated with ACE inhibitors. These patients presented with abdominal pain (with or without nausea or vomiting); in some cases there was no prior history of facial angioedema and C-1 esterase levels were normal. The angioedema was diagnosed by procedures including abdominal CT scan or ultrasound, or at surgery, and symptoms resolved after stopping the ACE inhibitor. Intestinal angioedema should be included in the differential diagnosis of patients on ACE inhibitors presenting with abdominal pain.

Anaphylactoid Reactions During Desensitization

Two patients undergoing desensitizing treatment with hymenoptera venom while receiving ACE inhibitors sustained life-threatening anaphylactoid reactions. In the same patients, these reactions did not occur when ACE inhibitors were temporarily withheld, but they reappeared when the ACE inhibitors were inadvertently readministered.

Anaphylactoid Reactions During Membrane Exposure

Anaphylactoid reactions have been reported in patients dialyzed with high-flux membranes and treated concomitantly with an ACE inhibitor. Anaphylactoid reactions have also been reported in patients undergoing low-density lipoprotein apheresis with dextran sulfate absorption.

Hypotension

univasc® can cause symptomatic hypotension, although, as with other ACE inhibitors, this is unusual in uncomplicated hypertensive patients treated with univasc® alone. Symptomatic hypotension was seen in 0.5% of patients given moexipril and led to discontinuation of therapy in about 0.25%. Symptomatic hypotension is most likely to occur in patients who have been salt- and volume-depleted as a result of prolonged diuretic therapy, dietary salt restriction, dialysis, diarrhea, or vomiting. Volume- and salt-depletion should be corrected and, in general, diuretics stopped, before initiating therapy with univasc® (see PRECAUTIONS, Drug Interactions, and ADVERSE REACTIONS).

In patients with congestive heart failure, with or without associated renal insufficiency, ACE inhibitor therapy may cause excessive hypotension, which may be associated with oliguria or progressive azotemia, and rarely, with acute renal failure and death. In these patients, univasc® therapy should be started under close medical supervision, and patients should be followed closely for the first two weeks of treatment and whenever the dose of moexipril or an accompanying diuretic is increased. Care in avoiding hypotension should also be taken in patients with ischemic heart disease, aortic stenosis, or cerebrovascular disease, in whom an excessive decrease in blood pressure could result in a myocardial infarction or a cerebrovascular accident.

If hypotension occurs, the patient should be placed in a supine position and, if necessary, treated with an intravenous infusion of normal saline. univasc® treatment usually can be continued following restoration of blood pressure and volume.

Neutropenia/Agranulocytosis

Another ACE inhibitor, captopril, has been shown to cause agranulocytosis and bone marrow depression, rarely in patients with uncomplicated hypertension, but more frequently in hypertensive patients with renal impairment, especially if they also have a collagen-vascular disease such as systemic lupus erythematosus or scleroderma. Although there were no instances of severe neutropenia (absolute neutrophil count <500/mm^3) among patients given univasc®, as with other ACE inhibitors, monitoring of white blood cell counts should be considered for patients who have collagen-vascular disease, especially if the disease is associated with impaired renal function. Available data from clinical trials of univasc® are insufficient to show that univasc® does not cause agranulocytosis at rates similar to captopril.

Fetal Toxicity

Pregnancy Category D

Use of drugs that act on the renin-angiotensin system during the second and third trimesters of pregnancy reduces fetal renal function and increases fetal and neonatal morbidity and death. Resulting oligohydramnios can be associated with fetal lung hypoplasia and skeletal deformations. Potential neonatal adverse effects include skull hypoplasia, anuria, hypotension, renal failure, and death. When pregnancy is detected, discontinue univasc® as soon as possible. These adverse outcomes are usually associated with use of these drugs in the second and third trimester of pregnancy. Most epidemiologic studies examining fetal abnormalities after exposure to antihypertensive use in the first trimester have not distinguished drugs affecting the renin-angiotensin system from other antihypertensive agents. Appropriate management of maternal hypertension during pregnancy is important to optimize outcomes for both mother and fetus.

In the unusual case that there is no appropriate alternative to therapy with drugs affecting the renin-angiotensin system for a particular patient, apprise the mother of the potential risk to the fetus. Perform serial ultrasound examinations to assess the intra-amniotic environment. If oligohydramnios is observed, discontinue univasc®, unless it is considered lifesaving for the mother. Fetal testing may be appropriate, based on the week of pregnancy. Patients and physicians should be aware, however, that oligohydramnios may not appear until after the fetus has sustained irreversible injury. Closely observe infants with histories of in utero exposure to univasc® for hypotension, oliguria, and hyperkalemia. (see Precautions, Pediatric Use).

No embryotoxic, fetotoxic, or teratogenic effects were seen in rats or in rabbits treated with up to 90.9 and 0.7 times, respectively, the Maximum Recommended Human Dose (MRHD) on a mg/m^2 basis.

Hepatic Failure

Rarely, ACE inhibitors have been associated with a syndrome that starts with cholestatic jaundice and progresses to fulminant hepatic necrosis and sometimes death. The mechanism of this syndrome is not understood. Patients receiving ACE inhibitors who develop jaundice or marked elevations of hepatic enzymes should discontinue the ACE inhibitor and receive appropriate medical follow-up.

PRECAUTIONS

General

Impaired Renal Function

As a consequence of inhibition of the renin-angiotensin-aldosterone system, changes in renal function may be anticipated in susceptible individuals. There is no clinical experience of univasc® in the treatment of hypertension in patients with renal failure.

Some hypertensive patients with no apparent preexisting renal vascular disease have developed increases in blood urea nitrogen and serum creatinine, usually minor and transient, especially when univasc® has been given concomitantly with a thiazide diuretic. This is more likely to occur in patients with preexisting renal impairment. There may be a need for dose adjustment of univasc® and/or the discontinuation of the thiazide diuretic.

Evaluation of hypertensive patients should always include assessment of renal function (see DOSAGE AND ADMINISTRATION).

Hypertensive Patients With Congestive Heart Failure

In hypertensive patients with severe congestive heart failure, whose renal function may depend on the activity of the renin-angiotensin-aldosterone system, treatment with ACE inhibitors, including univasc®, may be associated with oliguria and/or progressive azotemia and, rarely, acute renal failure and/or death.

Hypertensive Patients With Renal Artery Stenosis

In hypertensive patients with unilateral or bilateral renal artery stenosis, increases in blood urea nitrogen and serum creatinine have been observed in some patients following ACE inhibitor therapy. These increases were almost always reversible upon discontinuation of the ACE inhibitor and/or diuretic therapy. In such patients, renal function should be monitored during the first few weeks of therapy.

Hyperkalemia

In clinical trials, persistent hyperkalemia (serum potassium above 5.4 mEq/L) occurred in approximately 1.3% of hypertensive patients receiving univasc®. Risk factors for the development of hyperkalemia with ACE inhibitors include renal insufficiency, diabetes mellitus, and the concomitant use of potassium-sparing diuretics, potassium supplements, and/or potassium-containing salt substitutes, which should be used cautiously, if at all, with univasc® (see PRECAUTIONS, Drug Interactions).

Surgery/Anesthesia

In patients undergoing major surgery or during anesthesia with agents that produce hypotension, moexipril may block the effects of compensatory renin release. If hypotension occurs in this setting and is considered to be due to this mechanism, it can be corrected by volume expansion.

Cough

Presumably due to the inhibition of the degradation of endogenous bradykinin, persistent nonproductive cough has been reported with all ACE inhibitors, always resolving after discontinuation of therapy. ACE inhibitor-induced cough should be considered in the differential diagnosis of cough. In controlled trials with moexipril, cough was present in 6.1% of moexipril patients and 2.2% of patients given placebo.

Information for Patients

Food

Patients should be advised to take moexipril one hour before meals (see CLINICAL PHARMACOLOGY and DOSAGE AND ADMINISTRATION).

Angioedema

Angioedema, including laryngeal edema, may occur with treatment with ACE inhibitors, usually occurring early in therapy (within the first month). Patients should be so advised and told to report immediately any signs or symptoms suggesting angioedema (swelling of the face, extremities, eyes, lips, tongue, difficulty in breathing) and to take no more univasc® until they have consulted with the prescribing physician.

Symptomatic Hypotension

Patients should be cautioned that lightheadedness can occur with univasc®, especially during the first few days of therapy. If fainting occurs, the patient should stop taking univasc® and consult the prescribing physician.

All patients should be cautioned that excessive perspiration and dehydration may lead to an excessive fall in blood pressure because of reduction in fluid volume. Other causes of volume depletion such as vomiting or diarrhea may also lead to a fall in blood pressure; patients should be advised to consult their physician if they develop these conditions.

Hyperkalemia

Patients should be told not to use potassium supplements or salt substitutes containing potassium without consulting their physician.

Neutropenia

Patients should be told to report promptly any indication of infection (e.g., sore throat, fever) that could be a sign of neutropenia.

Pregnancy

Female patients of childbearing age should be told about the consequences of exposure to univasc® during pregnancy. Discuss treatment options with women planning to become pregnant. Patients should be asked to report pregnancies to their physicians as soon as possible.

Drug Interactions

Diuretics

Excessive reductions in blood pressure may occur in patients on diuretic therapy when ACE inhibitors are started. The possibility of hypotensive effects with univasc® can be minimized by discontinuing diuretic therapy for several days or cautiously increasing salt intake before initiation of treatment with univasc®. If this is not possible, the starting dose of moexipril should be reduced. (See WARNINGS and DOSAGE AND ADMINISTRATION).

Potassium Supplements and Potassium-Sparing Diuretics

univasc® can increase serum potassium because it decreases aldosterone secretion. Use of potassium-sparing diuretics (spironolactone, triamterene, amiloride) or potassium supplements concomitantly with ACE inhibitors can increase the risk of hyperkalemia. Therefore, if concomitant use of such agents is indicated, they should be given with caution and the patient's serum potassium should be monitored.

Oral Anticoagulants

Interaction studies with warfarin failed to identify any clinically important effect on the serum concentrations of the anticoagulant or on its anticoagulant effect.

Lithium

Increased serum lithium levels and symptoms of lithium toxicity have been reported in patients receiving ACE inhibitors during therapy with lithium. These drugs should be coadministered with caution, and frequent monitoring of serum lithium levels is recommended. If a diuretic is also used, the risk of lithium toxicity may be increased.

Gold

Nitritoid reactions (symptoms include facial flushing, nausea, vomiting, and hypotension) have been reported rarely in patients on therapy with injectable gold (sodium aurothiomalate) and concomitant ACE inhibitor therapy including univasc®.

Non-steroidal Anti-Inflammatory Agents including Selective Cyclooxygenase-2 Inhibitors (COX-2 Inhibitors)

In patients who are elderly, volume-depleted (including those on diuretic therapy), or with compromised renal function, co-administration of NSAIDS, including selective COX-2 inhibitors, with ACE inhibitors, including moexipril, may result in deterioration of renal function, including possible acute renal failure. These effects are usually reversible. Monitor renal function periodically in patients receiving moexipril and NSAID therapy.

The antihypertensive effect of ACE inhibitors, including moexipril, may be attenuated by NSAIDS.

Dual Blockade of the Renin-Angiotensin System (RAS)

Dual blockade of the RAS with angiotensin receptor blockers, ACE inhibitors, or aliskiren is associated with increased risks of hypotension, hyperkalemia, and changes in renal function (including acute renal failure) compared to monotherapy. Closely monitor blood pressure, renal function and electrolytes in patients on univasc® and other agents that affect the RAS.

Do not co-administer aliskiren with univasc® in patients with diabetes. Avoid use of aliskiren with univasc® in patients with renal impairment (GFR <60 mL/min).

Other Agents

No clinically important pharmacokinetic interactions occurred when univasc® was administered concomitantly with hydrochlorothiazide, digoxin, or cimetidine.

univasc® has been used in clinical trials concomitantly with calcium-channel-blocking agents, diuretics, H2 blockers, digoxin, oral hypoglycemic agents, and cholesterol-lowering agents. There was no evidence of clinically important adverse interactions.

Carcinogenesis, Mutagenesis, Impairment of Fertility

No evidence of carcinogenicity was detected in long-term studies in mice and rats at doses up to 14 or 27.3 times the Maximum Recommended Human Dose (MRHD) on a mg/m^2 basis.

No mutagenicity was detected in the Ames test and microbial reverse mutation assay, with and without metabolic activation, or in an in vivo nucleus anomaly test. However, increased chromosomal aberration frequency in Chinese hamster ovary cells was detected under metabolic activation conditions at a 20-hour harvest time.

Reproduction studies have been performed in rabbits at oral doses up to 0.7 times the MRHD on a mg/m^2 basis, and in rats up to 90.9 times the MRHD on a mg/m^2 basis. No indication of impaired fertility, reproductive toxicity, or teratogenicity was observed.

Nursing Mothers

It is not known whether univasc® is excreted in human milk. Because many drugs are excreted in human milk, caution should be exercised when univasc® is given to a nursing mother.

Pediatric Use

Neonates with a history of in utero exposure to univasc®

If oliguria or hypotension occurs, direct attention toward support of blood pressure and renal perfusion. Exchange transfusions or dialysis may be required as a means of reversing hypotension and/or substituting for disordered renal function.

Safety and effectiveness of univasc® in pediatric patients have not been established.

Geriatric Use

Clinical studies of univasc® did not include sufficient numbers of subjects aged 65 and over to determine whether they respond differently from younger subjects. Other reported clinical experience has not identified differences in responses between the elderly and younger patients. In general, dose selection for an elderly patient should be cautious, usually starting at the low end of the dosing range, reflecting the greater frequency of decreased hepatic, renal, or cardiac function, and of concomitant disease or other drug therapy.

ADVERSE REACTIONS

univasc® has been evaluated for safety in more than 2500 patients with hypertension; more than 250 of these patients were treated for approximately one year. The overall incidence of reported adverse events was only slightly greater in patients treated with univasc® than patients treated with placebo.

Reported adverse experiences were usually mild and transient, and there were no differences in adverse reaction rates related to gender, race, age, duration of therapy, or total daily dosage within the range of 3.75 mg to 60 mg. Discontinuation of therapy because of adverse experiences was required in 3.4% of patients treated with univasc® and in 1.8% of patients treated with placebo. The most common reasons for discontinuation in patients treated with univasc® were cough (0.7%) and dizziness (0.4%).

All adverse experiences considered at least possibly related to treatment that occurred at any dose in placebo-controlled trials of once-daily dosing in more than 1% of patients treated with univasc® alone and that were at least as frequent in the univasc® group as in the placebo group are shown in the following table:

ADVERSE EVENTS IN PLACEBO-CONTROLLED STUDIES
ADVERSE EVENT | UNIVASC (N=674) | PLACEBO (N=226)
 | N (%) | N (%)
Cough Increased | 41 (6.1) | 5 (2.2)
Dizziness | 29 (4.3) | 5 (2.2)
Diarrhea | 21 (3.1) | 5 (2.2)
Flu Syndrome | 21 (3.1) | 0 (0)
Fatigue | 16 (2.4) | 4 (1.8)
Pharyngitis | 12 (1.8) | 2 (0.9)
Flushing | 11 (1.6) | 0 (0)
Rash | 11 (1.6) | 2 (0.9)
Myalgia | 9 (1.3) | 0 (0)

Other adverse events occurring in more than 1% of patients on moexipril that were at least as frequent on placebo include: headache, upper respiratory infection, pain, rhinitis, dyspepsia, nausea, peripheral edema, sinusitis, chest pain, and urinary frequency. See WARNINGS and PRECAUTIONS for discussion of anaphylactoid reactions, angioedema, hypotension, neutropenia/agranulocytosis, second and third trimester fetal/neonatal morbidity and mortality, hyperkalemia, and cough.

Other potentially important adverse experiences reported in controlled or uncontrolled clinical trials in less than 1% of moexipril patients or that have been attributed to other ACE inhibitors include the following:

Cardiovascular: Symptomatic hypotension, postural hypotension, or syncope were seen in 9/1750 (0.51%) patients; these reactions led to discontinuation of therapy in controlled trials in 3/1254 (0.24%) patients who had received univasc® monotherapy and in 1/344 (0.3%) patients who had received univasc® with hydrochlorothiazide (see PRECAUTIONS and WARNINGS). Other adverse events included angina/myocardial infarction, palpitations, rhythm disturbances, and cerebrovascular accident.

Renal: Of hypertensive patients with no apparent preexisting renal disease, 1% of patients receiving univasc® alone and 2% of patients receiving univasc® with hydrochlorothiazide experienced increases in serum creatinine to at least 140% of their baseline values (see PRECAUTIONS and DOSAGE AND ADMINISTRATION).

Gastrointestinal: Abdominal pain, constipation, vomiting, appetite/weight change, dry mouth, pancreatitis, hepatitis.

Respiratory: Bronchospasm, dyspnea, eosinophilic pneumonitis.

Urogenital: Renal insufficiency, oliguria.

Dermatologic: Apparent hypersensitivity reactions manifested by urticaria, rash, pemphigus, pruritus, photosensitivity, alopecia.

Neurological and Psychiatric: Drowsiness, sleep disturbances, nervousness, mood changes, anxiety.

Other: Angioedema (see WARNINGS), taste disturbances, tinnitus, sweating, malaise, arthralgia, hemolytic anemia.

Clinical Laboratory Test Findings

Serum Electrolytes

Hyperkalemia (see PRECAUTIONS), hyponatremia.

Creatinine and Blood Urea Nitrogen

As with other ACE inhibitors, minor increases in blood urea nitrogen or serum creatinine, reversible upon discontinuation of therapy, were observed in approximately 1% of patients with essential hypertension who were treated with univasc®. Increases are more likely to occur in patients receiving concomitant diuretics and in patients with compromised renal function (see PRECAUTIONS, General).

Other (causal relationship unknown)

Clinically important changes in standard laboratory tests were rarely associated with univasc® administration.

Elevations of liver enzymes and uric acid have been reported. In trials, less than 1% of moexipril-treated patients discontinued univasc® treatment because of laboratory abnormalities. The incidence of abnormal laboratory values with moexipril was similar to that in the placebo-treated group.

OVERDOSAGE

Human overdoses of moexipril have not been reported. In case reports of overdoses with other ACE inhibitors, hypotension has been the principal adverse effect noted. Single oral doses of 2 g/kg moexipril were associated with significant lethality in mice. Rats, however, tolerated single oral doses of up to 3 g/kg.

No data are available to suggest that physiological maneuvers (e.g., maneuvers to change the pH of the urine) would accelerate elimination of moexipril and its metabolites. The dialyzability of moexipril is not known.

Angiotensin II could presumably serve as a specific antagonist-antidote in the setting of moexipril overdose, but angiotensin II is essentially unavailable outside of research facilities. Because the hypotensive effect of moexipril is achieved through vasodilation and effective hypovolemia, it is reasonable to treat moexipril overdose by infusion of normal saline solution. In addition, renal function and serum potassium should be monitored.

DOSAGE AND ADMINISTRATION

Hypertension

The recommended initial dose of univasc® in patients not receiving diuretics is 7.5 mg, one hour prior to meals, once daily. Dosage should be adjusted according to blood pressure response. The antihypertensive effect of univasc® may diminish towards the end of the dosing interval. Blood pressure should, therefore, be measured just prior to dosing to determine whether satisfactory blood pressure control is obtained. If control is not adequate, increased dose or divided dosing can be tried. The recommended dose range is 7.5 to 30 mg daily, administered in one or two divided doses one hour before meals. Total daily doses above 60 mg a day have not been studied in hypertensive patients.

In patients who are currently being treated with a diuretic, symptomatic hypotension may occasionally occur following the initial dose of univasc®. The diuretic should, if possible, be discontinued for 2 to 3 days before therapy with univasc® is begun, to reduce the likelihood of hypotension (see WARNINGS). If the patient's blood pressure is not controlled with univasc® alone, diuretic therapy may then be reinstituted. If diuretic therapy cannot be discontinued, an initial dose of 3.75 mg of univasc® should be used with medical supervision until blood pressure has stabilized (see WARNINGS and PRECAUTIONS, Drug Interactions).

Dosage Adjustment in Renal Impairment

For patients with a creatinine clearance ≤40 mL/min/1.73 m^2, an initial dose of 3.75 mg once daily should be given cautiously. Doses may be titrated upward to a maximum daily dose of 15 mg.

HOW SUPPLIED

univasc® (moexipril hydrochloride) 7.5 mg tablets are pink colored, biconvex, film-coated and scored with engraved code 707 on the unscored side and SP above and 7.5 below the score. They are supplied as follows:

Bottles of 90 (Unit-of-Use) | NDC 0091-3707-09
Bottles of 100 | NDC 0091-3707-01

univasc® (moexipril hydrochloride) 15 mg tablets are salmon colored, biconvex, film-coated, and scored with engraved code 715 on the unscored side and SP above and 15 below the score. They are supplied as follows:

Bottles of 90 (Unit-of-Use) | NDC 0091-3715-09
Bottles of 100 | NDC 0091-3715-01

Store, tightly closed, at controlled room temperature 20° to 25°C (68° to 77°F). Protect from excessive moisture.

If product package is subdivided, dispense in tight containers as described in USP-NF.

Manufactured for:
UCB, Inc.
Smyrna, GA 30080

Rev. 5E 09/2012

PRINCIPAL DISPLAY PANEL - 7.5 mg Tablets Bottle Label

NDC 0091-3707-01

univasc® tablets
(moexipril HCl)

7.5 mg

Rx only

100 tablets

PRINCIPAL DISPLAY PANEL - 15 mg Tablets Bottle Label

NDC 0091-3715-01

univasc® tablets
(moexipril HCl)

15 mg

Rx only

100 tablets